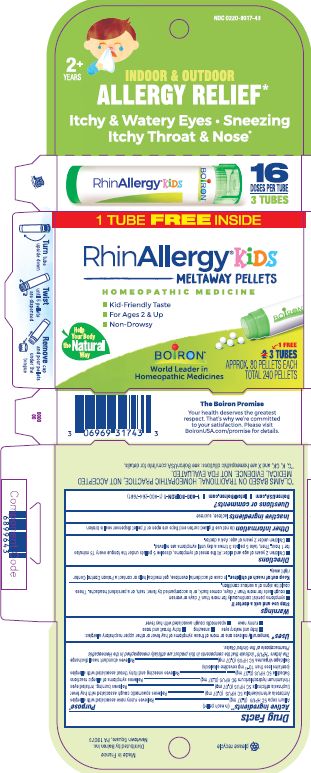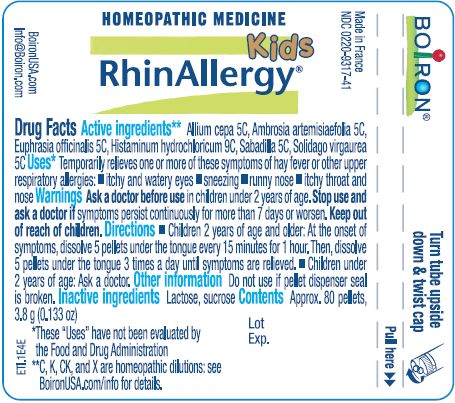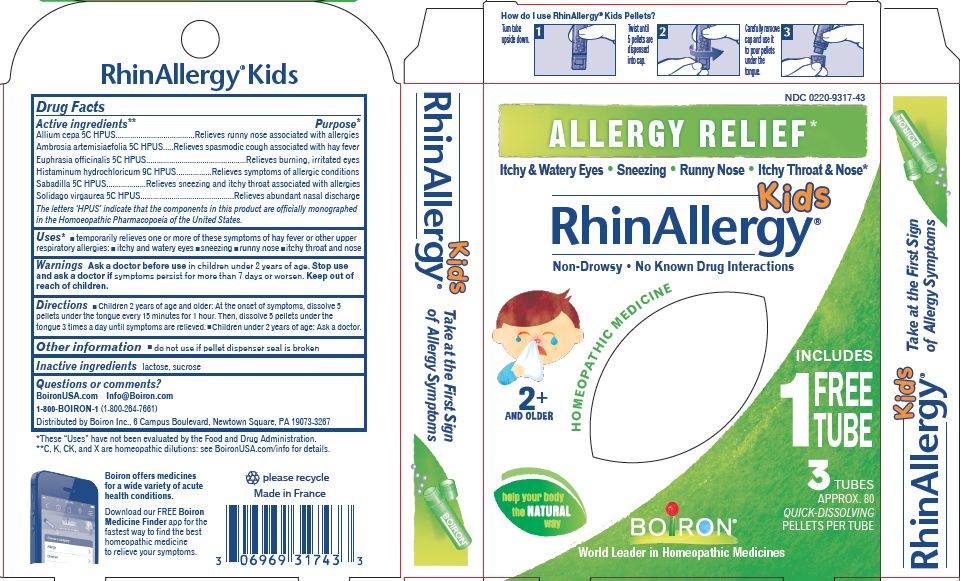 DRUG LABEL: RhinAllergy Kids
NDC: 0220-9317 | Form: PELLET
Manufacturer: Boiron
Category: homeopathic | Type: HUMAN OTC DRUG LABEL
Date: 20201211

ACTIVE INGREDIENTS: ONION 5 [hp_C]/1 1; SCHOENOCAULON OFFICINALE SEED 5 [hp_C]/1 1; SOLIDAGO VIRGAUREA FLOWERING TOP 5 [hp_C]/1 1; HISTAMINE DIHYDROCHLORIDE 9 [hp_C]/1 1; AMBROSIA ARTEMISIIFOLIA 5 [hp_C]/1 1; EUPHRASIA STRICTA 5 [hp_C]/1 1
INACTIVE INGREDIENTS: SUCROSE; LACTOSE, UNSPECIFIED FORM

RhinAllergy Kids Pellets

ACTIVE INGREDIENT

Allium cepa 5C HPUS (0.07 mg)**

Ambrosia artemisiaefolia 5C HPUS (0.07 mg)**

Euphrasia officinalis 5C HPUS (0.07 mg)**

Histaminum hydrochloricum 9C HPUS (0.07 mg)**

Sabadilla 5C HPUS (0.07 mg)** (contains less than 10^-13 mg cevadine alkaloids)

Solidago virgaurea 5C HPUS (0.07 mg)**

(in each pellet)

The letters "HPUS" indicate that the components in this product are officially monographed in the Homeopathic Pharmacopoeia of the United States.

PURPOSE

Allium cepa 5C HPUS........relieves runny nose associated with allergies*

Ambrosia artemisiaefolia 5C HPUS......relieves spasmodic cough associated with hay fever*

Euphrasia officinalis 5C HPUS......relieves burning, irritated eyes*

Histaminum hydrochloricum 9C HPUS......relieves symptoms of allergic conditions*

Sabadilla 5C HPUS......relieves sneezing and itchy throat associated with allergies*

Solidago virgaurea 5C HPUS......relieves abundant nasal discharge*

INDICATIONS AND USAGE

temporarily relieves one or more of these symptoms of hay fever or other upper respiratory allergies:

- itchy and watery eyes
- sneezing
- runny nose
- itchy throat and nose
- spasmodic cough associated with hay fever

ASK DOCTOR/PHARMACIST

NA

STOP USE

NA

Stop use and ask a doctor if

- symptoms persist continuously for more than 7 days or worsen
- cough lasts for more than 7 days, comes back, or is accompanied by fever, rash, or a persistent headache. These could be signs of a serious condition.

PREGNANCY OR BREAST FEEDING

NA product is for children

Keep out of reach of children. In case of accidental overdose, get medical help or contact a Poison Control Center right away.

DOSAGE AND ADMINISTRATION

Children 2 years of age and older:

- At the onset of symptoms, dissolve 5 pellets under the tongue every 15 minutes for 1 hour. Then, take 5 pellets 3 times a day until symptoms are relieved.
- Children under 2 years of age: Ask a doctor.

do not use if glued carton end flaps are open or if pellet dispenser seal is broken

3 Tubes

Approx. 80 Pellets Each

Total 240 Pellets

16 Doses per tube

Turn tube upside down

Twist until 5 pellets are dispensed

Remove cap and pour pellets under the tongue

*CLAIMS BASED ON TRADITIONAL HOMEOPATHIC PRACTICE, NOT ACCEPTED MEDICAL EVIDENCE. NOT FDA EVALUATED.
*C,K,CK, and X are homeopathic dilutions: see BoironUSA.com/info for details.

INACTIVE INGREDIENT

lactose, sucrose

QUESTIONS

info@boironusa.com

BoironUSA.com
1-800-BOIRON-1 (1-800-264-7661),

Distributed by Boiron, Inc.

Newtown Square, PA 19073

NA